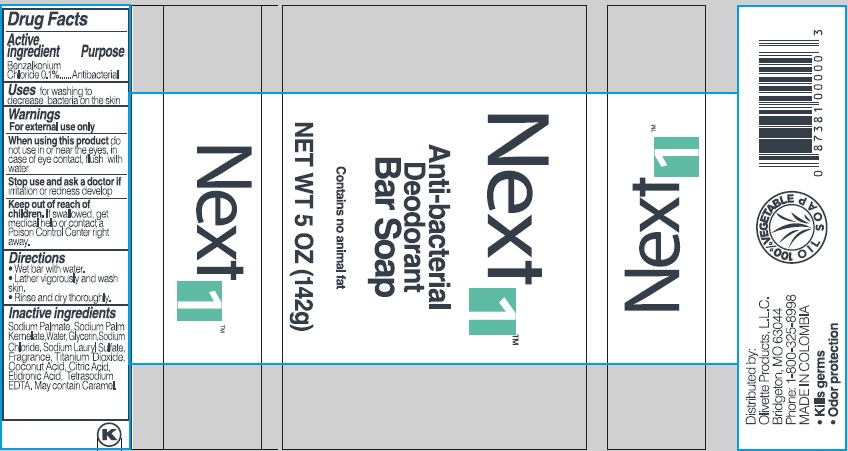 DRUG LABEL: Next 1 Anti-bacterial Deodorant
NDC: 51870-004 | Form: SOAP
Manufacturer: Keefe Group
Category: otc | Type: HUMAN OTC DRUG LABEL
Date: 20240101

ACTIVE INGREDIENTS: BENZALKONIUM CHLORIDE 0.1 g/100 g
INACTIVE INGREDIENTS: SODIUM PALM KERNELATE; SODIUM LAURYL SULFATE; EDETATE SODIUM; CARAMEL; TITANIUM DIOXIDE; GLYCERIN; SODIUM CHLORIDE; COCONUT ACID; CITRIC ACID MONOHYDRATE; ETIDRONIC ACID; WATER; SODIUM PALMATE

Next 1TM Anti-bacterial Deodorant Bar Soap

Drug Facts

Active ingredient

Benzalkonium Chloride 0.1%

Purpose

Antibacterial

Uses

for washing to decrease bacteria on the skin

Warnings

For external use only

When using this product do not use in or near the eyes, in case of eye contact, flush with water

Stop use and ask a doctor if irritation or redness develop

Keep out of reach of children. If swallowed, get medical help or contact a Poison Control Center right away.

Directions

- Web bar with water.
- Lather vigorously and wash skin.
- Rinse and dry thoroughly.

INACTIVE INGREDIENT

Inactive ingredients Sodium Palmate, Sodium Palm Kernelate, Water, Glycerin, Sodium Chloride, Sodium Lauryl Sulfate, Fragrance, Titanium Dioxide, Coconut Acid, Citric Acid, Etidronic Acid, Tetrasodium EDTA. May contain Caramel.

Distributed by:

Olivette Products, L.L.C.

Bridgeton, MO 63044

Phone: 1-800-325-8998

MADE IN COLOMBIA

- Kills germs
- Odor protection

PACKAGE LABEL

Next 1TM

Anti-bacterial

Deodorant

Bar Soap

Contains no animal fat

NET WT 5 OZ (142g)